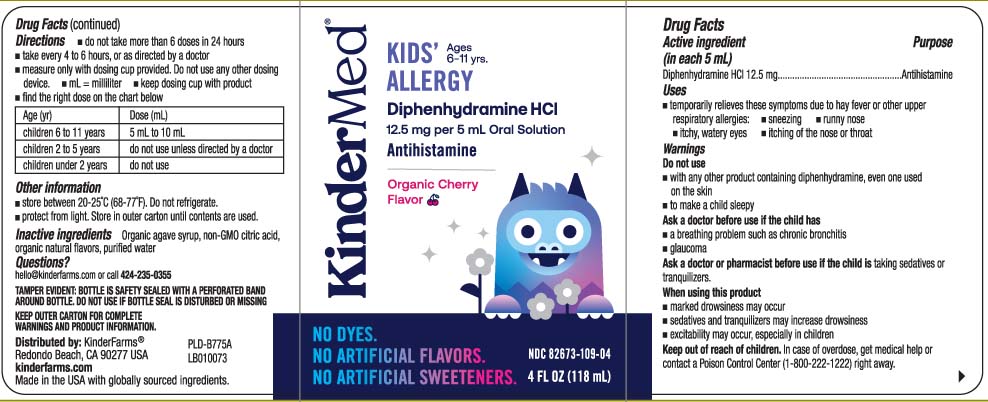 DRUG LABEL: Childrens Allergy
NDC: 82673-109 | Form: LIQUID
Manufacturer: KinderFarms, LLC
Category: otc | Type: HUMAN OTC DRUG LABEL
Date: 20241004

ACTIVE INGREDIENTS: DIPHENHYDRAMINE HYDROCHLORIDE 12.5 mg/5 mL
INACTIVE INGREDIENTS: CITRIC ACID MONOHYDRATE; AGAVE TEQUILANA JUICE; WATER

Drug Facts

Active ingredient (in each 5 mL)

Diphenhydramine HCl 12.5 mg

Purpose

Antihistamine

Uses

- temporarily relieves these symptoms due to hay fever or other upper respiratory allergies:
  - runny nose
  - sneezing
  - itchy, watery eyes
  - itching of the nose or throat

Warnings

Do not use

- with any other product containing diphenhydramine, even one used on skin
- to make a child sleepy

Ask a doctor before use if the child has

- a breathing problem such as chronic bronchitis
- glaucoma

Ask a doctor or pharmacist before use if the child is

taking sedatives or tranquilizers.

When using this product

- marked drowsiness may occur
- sedatives and tranquilizers may increase drowsiness
- excitability may occur, especially in children

Keep out of the reach of children.

In case of overdose, get medical help or contact a Poison Control Center (1-800-222-1222) right away.

Directions

- do not take more than 6 doses in 24 hours
- take every 4 to 6 hours, or as directed by a doctor
- measure only with dosing cup provided. Do not use any other dosing device.
- mL = milliliter
- keep dosing cup with product
- find the right dose on chart below

age (yrs) | dose (mL)
children 6 to 11 years | 5 mL to 10 mL
children 2 to 5 years | do not use unless directed by a doctor
children under 2 years | do not use

Other information

- store between 20-25ºC (68-77ºF). Do not refrigerate.
- protect from light. Store in outer carton until contents are used

Inactive ingredient

Organic agave syrup, non-GMO citric acid, organic natural flavor, purified water

Questions or comments?

Call 424-235-0355

Principal Display Panel

KIDS' Ages 6-11 yrs

ALLERGY

Diphenhydramine HCl

12.5 mg per 5 mL Oral Solution

Antihistamine

Organic Cherry Flavor

FL OZ (mL)

DOSAGE CUP PROVIDED

TAMPER EVIDENT: BOTTLE IS SAFETY SEALED WITH A PERFORATED BAND AROUND BOTTLE. DO NOT USE IF BOTTLE SEAL IS DISTURBED OR MISSING.

KEEP OUTER CARTON FOR COMPLETE WARNINGS AND PRODUCT INFORMATION.

Distributed by: KinderFarms®

Redondo Beach, CA 90277 USA

Product Label

KINDERMED Kids Allergy Organic Cherry Flavor